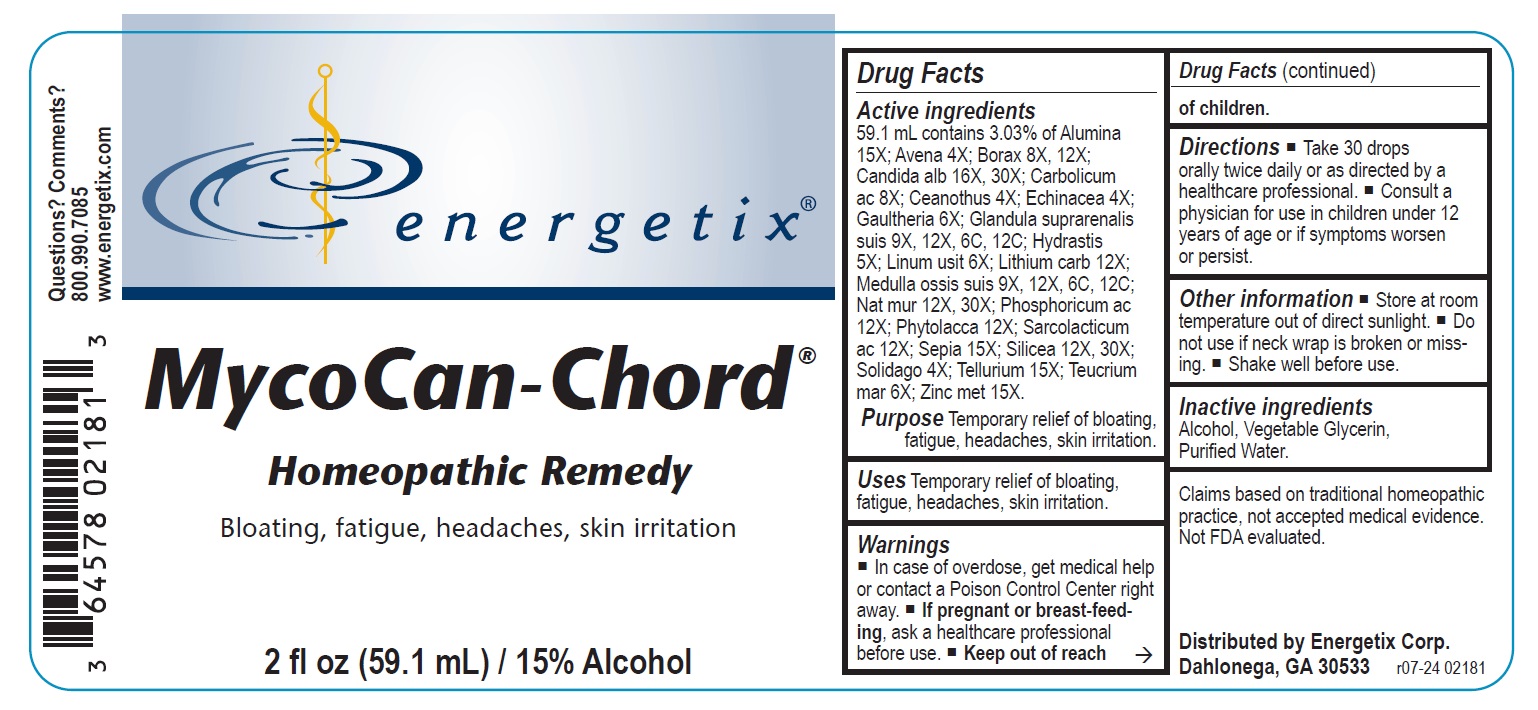 DRUG LABEL: MycoCan-Chord
NDC: 64578-0144 | Form: LIQUID
Manufacturer: Energetix Corporation
Category: homeopathic | Type: HUMAN OTC DRUG LABEL
Date: 20241120

ACTIVE INGREDIENTS: ALUMINUM OXIDE 15 [hp_X]/59.1 mL; AVENA SATIVA FLOWERING TOP 4 [hp_X]/59.1 mL; SODIUM BORATE 8 [hp_X]/59.1 mL; CANDIDA ALBICANS 16 [hp_X]/59.1 mL; PHENOL 8 [hp_X]/59.1 mL; CEANOTHUS AMERICANUS LEAF 4 [hp_X]/59.1 mL; ECHINACEA ANGUSTIFOLIA 4 [hp_X]/59.1 mL; GAULTHERIA PROCUMBENS TOP 6 [hp_X]/59.1 mL; SUS SCROFA ADRENAL GLAND 9 [hp_X]/59.1 mL; GOLDENSEAL 5 [hp_X]/59.1 mL; FLAX SEED 6 [hp_X]/59.1 mL; LITHIUM CARBONATE 12 [hp_X]/59.1 mL; SUS SCROFA BONE MARROW 9 [hp_X]/59.1 mL; SODIUM CHLORIDE 12 [hp_X]/59.1 mL; PHOSPHORIC ACID 12 [hp_X]/59.1 mL; PHYTOLACCA AMERICANA ROOT 12 [hp_X]/59.1 mL; LACTIC ACID, L- 12 [hp_X]/59.1 mL; SEPIA OFFICINALIS JUICE 15 [hp_X]/59.1 mL; SILICON DIOXIDE 12 [hp_X]/59.1 mL; SOLIDAGO VIRGAUREA FLOWERING TOP 4 [hp_X]/59.1 mL; TELLURIUM 15 [hp_X]/59.1 mL; TEUCRIUM MARUM 6 [hp_X]/59.1 mL; ZINC 15 [hp_X]/59.1 mL
INACTIVE INGREDIENTS: WATER; GLYCERIN; ALCOHOL

MycoCan-Chord

ACTIVE INGREDIENT

Active ingredients 59.1 mL contains 3.03% of: Alumina 15X; Avena sativa 4X; Borax 8X, 12X; Candida alb 16X, 30X; Carbolicum ac 8X; Ceanothus 4X; Echinacea 4X; Gaultheria 6X; Glandula suprarenalis suis 9X, 12X, 6C, 12C; Hydrastis 5X; Linum usit 6X; Lithium carb 12X; Medulla ossis suis 9X, 12X, 6C, 12C; Nat mur 12X, 30X; Phosphoricum ac 12X; Phytolacca 12X; Sarcolacticum ac 12X; Sepia 15X; Silicea 12X, 30X; Solidago 4X; Tellurium 5X; Teucrium mar 6X; Zinc met 15X.

Claims based on traditional homeopathic practice, not accepted medical evidence. Not FDA evaluated.

Uses

Temporary relief of bloating, fatigue, headaches, , skin irritation.

Warnings

- In case of overdose, get medical help or contact a Poison Control Center right away.
- If pregnant or breast-feeding, ask a healthcare professional before use.

- Keep out of reach of children.

Uses

Temporary relief of bloating, fatigue, headaches, white-coated tongue, skin irritation.

Directions

- Take 30 drops orally twice daily or as directed by a healthcare professional.
- Consult a physician for use in children under 12 years of age or if symptoms worsen or persist.

Other information

- Store at room temperature out of direct sunlight.
- Do not use if neck wrap is broken or missing.
- Shake well before use.

Inactive ingredients Alcohol, Vegetable Glycerin, Purified Water.

QUESTIONS

Distributed by Energetix Corp.
Dahlonega, GA 30533
Questions? Comments?
800.990.7085
www.energetix.com

PACKAGE LABEL

energetix

MycoCan-Chord

Homeopathic Remedy

Bloating, fatigue, headaches, skin irritation

2 fl oz (59.1 mL) / 15% Alcohol

PURPOSE

Purpose Temporary relief of bloating, fatigue, headaches, skin irritation.